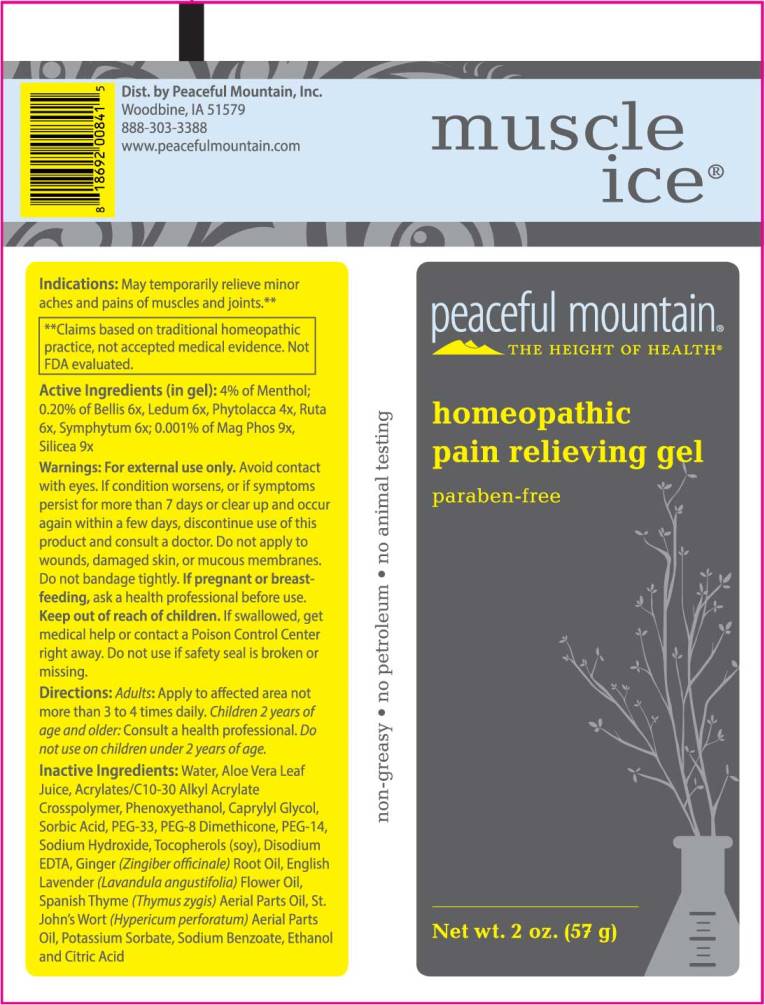 DRUG LABEL: Muscle Ice
NDC: 43846-0073 | Form: GEL
Manufacturer: Peaceful Mountain, Inc.
Category: homeopathic | Type: HUMAN OTC DRUG LABEL
Date: 20240613

ACTIVE INGREDIENTS: PHYTOLACCA AMERICANA ROOT 4 [hp_X]/1 g; BELLIS PERENNIS WHOLE 6 [hp_X]/1 g; LEDUM PALUSTRE TWIG 6 [hp_X]/1 g; RUTA GRAVEOLENS FLOWERING TOP 6 [hp_X]/1 g; COMFREY ROOT 6 [hp_X]/1 g; MAGNESIUM PHOSPHATE, DIBASIC TRIHYDRATE 9 [hp_X]/1 g; SILICON DIOXIDE 9 [hp_X]/1 g
INACTIVE INGREDIENTS: MENTHOL; WATER; PHENOXYETHANOL; CAPRYLYL GLYCOL; SORBIC ACID; SODIUM HYDROXIDE; POLYETHYLENE GLYCOL 1600; PEG-8 DIMETHICONE; POLYETHYLENE GLYCOL 700; CARBOMER INTERPOLYMER TYPE A (ALLYL SUCROSE CROSSLINKED); TOCOPHEROL; ALOE VERA LEAF; EDETATE DISODIUM; POTASSIUM SORBATE; SPANISH THYME OIL; GINGER OIL; LAVENDER OIL; HYPERICUM OIL; ALCOHOL; CITRIC ACID MONOHYDRATE; SODIUM BENZOATE

DRUG FACTS:

ACTIVE INGREDIENTS:

(in gel): 4% of Menthol; 0.20% of Bellis 6X, Ledum Palustre 6X, Phytolacca Decandra 4X, Ruta Graveolens 6X, Symphytum Officinale 6X; 0.001% of Magnesia Phosphorica 9X, Silicea 9X.

INDICATIONS:

May temporarily relieve minor aches and pains of muscles and joints.**

**Claims based on traditional homeopathic principles, not accepted medical evidence. Not FDA evaluated.

WARNINGS:

For external use only. Avoid contact with eyes.

If condition worsens, or if symptoms persist for more than 7 days or clear up and occur again within a few days, discontinue use of this product and consult a doctor.

Do not apply to wounds or damaged skin, or mucous membranes. Do not bandage tightly.

If pregnant or breast-feeding, ask a health professional before use.

Keep out of reach of children. If swallowed, get medical help or contact a Poison Control Center right away. Do not use if saftey seal is broken or missing.

Keep out of reach of children. If swallowed, get medical help or contact a Poison Control Center right away.

DIRECTIONS:

Adults:Apply to affected area not more than 3 to 4 times daily.

Children 2 years of age and older: Consult a health professional. Do not use on children under 2 years of age.

INDICATIONS:

May temporarily relieve minor aches and pains of muscles and joints.**

**Claims based on traditional homeopathic principles, not accepted medical evidence. Not FDA evaluated.

INACTIVE INGREDIENTS:

Purified Water, Aloe Vera Leaf Juice, Acrylates/C10-30 Alkyl Acrylate Crosspolymer, Phenoxyethanol, Caprylyl Glycol, Sorbic Acid, PEG-33, PEG-8 Dimethicone, PEG-14, Sodium Hydroxide (Solution), Tocopherols (Derived from Soy Bean), EDETATE Disodium (EDTA), Ginger (Zingiber Officinale) Root Oil, English Lavender (Lavandula Angustifolia) Flower Oil, Spanish Thyme (Thymus Zygis) Aerial Parts Oil, St. John’s Wort (Hypericum Perforatum) Aerial Parts Oil, Potassium Sorbate, Sodium Benzoate, Ethanol and Citric Acid.

QUESTIONS

Dist. by Peaceful Mountain, Inc.

Woodbine, IA 51579

888-303-3388

www.peacefulmountain.com

PACKAGE LABEL DISPLAY:

muscle ice

peaceful mountain

THE HEIGHT OF HEALTH

homeopathic

pain relieving gel

paraben-free

Net wt. 2 oz (57 g)